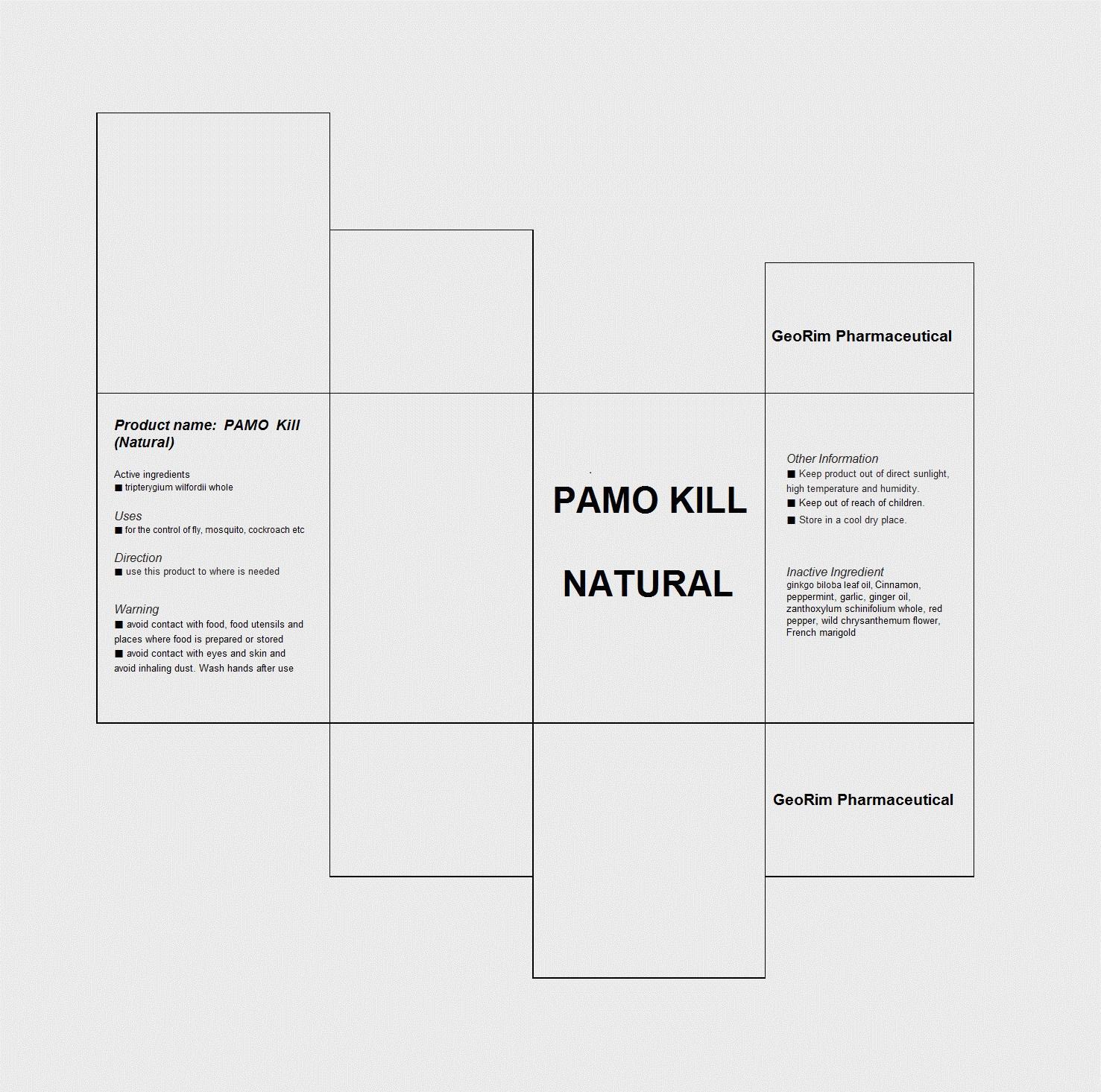 DRUG LABEL: PAMO Kill Natural
NDC: 59494-2001 | Form: LIQUID
Manufacturer: GeoRim Pharmaceutical
Category: otc | Type: HUMAN OTC DRUG LABEL
Date: 20131007

ACTIVE INGREDIENTS: TRIPTERYGIUM WILFORDII WHOLE 28 g/100 mL
INACTIVE INGREDIENTS: CINNAMON; GINKGO BILOBA LEAF OIL; GARLIC OIL; GINGER OIL; ZANTHOXYLUM SCHINIFOLIUM WHOLE; RED PEPPER; DENDRANTHEMA INDICUM FLOWER

Drug Facts

ACTIVE INGREDIENT

tripterygium wilfordii whole

INACTIVE INGREDIENT

ginkgo biloba leaf oil, cinnamon, peppermint, garlic, ginger oil, zanthoxylum schinifolium whole, red pepper, wild chrysanthemum flower, french marigold

PURPOSE

for the control of fly, mosquito cockroach etc

keep out or reach of the children

INDICATIONS AND USAGE

spray to where is needed

WARNINGS

avoid contact with food, food, utensils and places where food is prepared or stored
avoid contact with eyes and skin and avoid inhaling dust. wash hands after use

DOSAGE AND ADMINISTRATION

for external use only